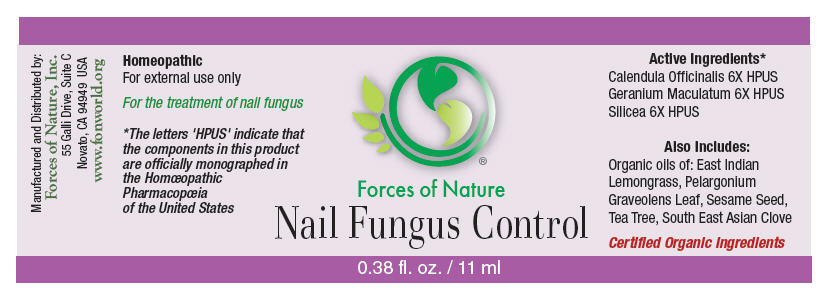 DRUG LABEL: Nail Fungus Control
NDC: 51393-6888 | Form: SOLUTION/ DROPS
Manufacturer: Forces of Nature
Category: homeopathic | Type: HUMAN OTC DRUG LABEL
Date: 20160613

ACTIVE INGREDIENTS: CALENDULA OFFICINALIS FLOWERING TOP 6 [hp_X]/1000 mL; SILICON DIOXIDE 6 [hp_X]/1000 mL
INACTIVE INGREDIENTS: Tea Tree Oil; GERANIUM OIL, ALGERIAN TYPE; EAST INDIAN LEMONGRASS OIL; Sesame Oil; Clove Oil

Nail Fungus Control

Drug Facts

Indications

For the temporary relief of pain, soreness and inflammation around nails.

ACTIVE INGREDIENT

PURPOSE

Homeopathic Active Ingredients [The letters 'HPUS' indicate that the components in this product are officially monographed in the Homœopathic Pharmacopœia of the United States.]
Equal parts of: | Purpose
Calendula Officinalis 6X HPUS | Promotes healthy skin and healing
Geranium Maculatum 6X HPUS | Heals ulcers in skin
Silicea 6X HPUS | Remedy for nail ulcers, fowl smelling, crippled nails

Inactive Ingredients

East Indian Lemongrass Oil, Pelargonium Graveolens Leaf Oil, Sesame Seed Oil, Tea Tree Oil, South East Asian Clove Oil

Directions

Wash and thoroughly dry the affected area. Apply 1-2 drops of the product and gently rub in. Wash your hands afterwards. Apply 3 times per day.

Warnings

STOP USE

If symptoms worsen, or redness or skin irritation occurs, discontinue product. Some individuals may be sensitive to tea tree or other oils. Begin with a small drop to determine if the product causes any increased redness or irritation and discontinue use if it irritates your skin.

PREGNANCY OR BREAST FEEDING

If you are pregnant or breast-feeding, ask a health professional before use.

KEEP OUT OF REACH OF CHILDREN

Keep out of the reach of children. If accidental ingestion, get medical help or contact a Poison Control Center.

DO NOT USE

For external use only. Do not apply to the eyes or mucous membranes. Keep all medicines out of the reach of children.

Product Note: Nail Fungus infections may begin as a white or yellow spot under the tip of your fingernail or toenail. As the nail fungus spreads deeper into your nail, it may cause your nail to discolor, thicken and develop crumbling edges. If condition worsens consult a physician.

Manufactured by:
Forces of Nature, Inc.
55 Galli Drive, Suite C
Novato, CA 94949 USA
www.fonworld.org

Product questions?

877-975-3797

NDC #: 51393-6888-1 (11ml) // 51393-6888-2 (33ml)

PRINCIPAL DISPLAY PANEL - 11 ml Bottle Label

Forces of Nature

Nail Fungus Control

0.38 fl. oz. / 11 ml